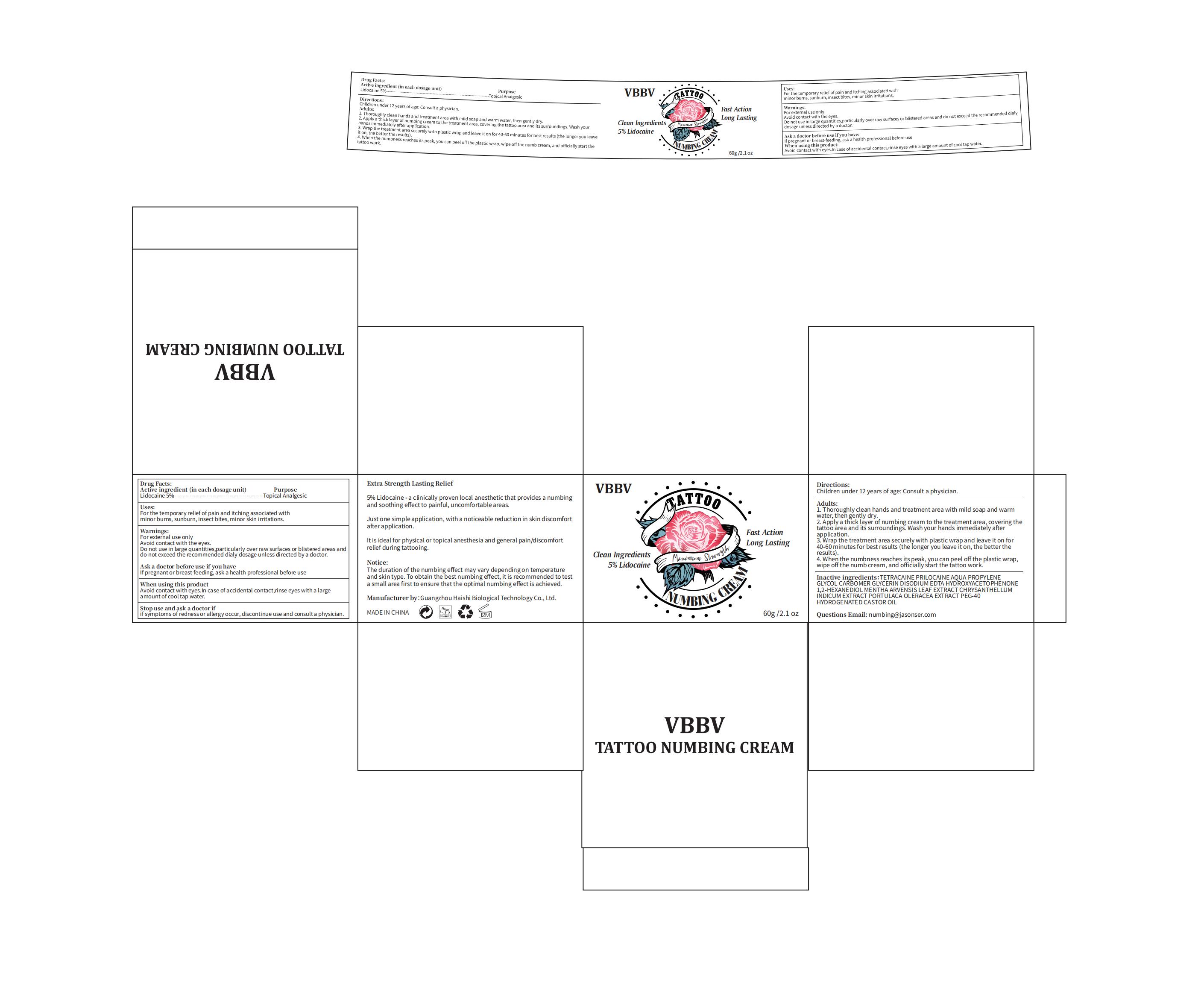 DRUG LABEL: VBBV Numbing cream
NDC: 60771-0005 | Form: CREAM
Manufacturer: Guangzhou Haishi Biological Technology Co., Ltd.
Category: otc | Type: HUMAN OTC DRUG LABEL
Date: 20241016

ACTIVE INGREDIENTS: LIDOCAINE 5 g/100 g
INACTIVE INGREDIENTS: HYDROXYACETOPHENONE; 1,2-HEXANEDIOL; GLYCERIN

VBBV Numbing cream

Active ingredients

Lidocaine 5%

Purpose

Topical Analgesic

Uses

1. Thoroughly clean hands and treatment area with mild soap and warm water, then gently dry.
2. Apply a thick layer of numbing cream to the treatment area, covering the tattoo area and its surroundings. Wash your hands immediately after
application:
3. Wrap the treatment area securely with plastic wrap and leave it on for 40-60 minutes for best results (the longer you leave it on, the better the results).
4. When the numbness reaches its peak, you can peel off the plastic wrap, wipe off the numb cream, and officially start the tattoo work.

Warnings

For external use only
Avoid contact with the eyes.
Do not use in large quantities,particularly over raw surfaces or blistered areas and
do not exceed the recommended dialy dosage unless directed by a doctor.

Stop Use

If symptoms of redness or allergy occur, discontinue use and consult a physician.

Do not use

on damaged or broken skin.

When Using

Avoid contact with eyes.In case of accidental contact,rinse eyes with a large
amount of cool tap water.

KEEP OUT OF REACH OF CHILDREN

Children under 12 years of age: Consult a physician.

Dosage

Apply a thick layer of numbing cream to the treatment area, covering the tattoo area and its surroundings.

Inactive ingredients

AQUA 73%
PROPYLENE GLYCOL 4%
CARBOMER 0.3%
GLYCERIN 5%
DISODIUM EDTA 0.05%
HYDROXYACETOPHENONE 0.5%
1,2-HEXANEDIOL 0.4%
MENTHA ARVENSIS LEAF EXTRACT 3.05%
CHRYSANTHELLUM INDICUM EXTRACT 3.5%
PORTULACA OLERACEA EXTRACT 3%
PEG-40 HYDROGENATED CASTOR OIL 0.2%
Tetracaine 1%
Prilocaine 1%